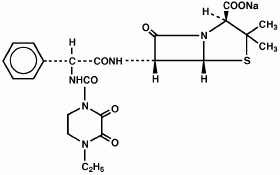 DRUG LABEL: Unknown
Manufacturer: Wyeth Pharmaceuticals, Inc.
Category: prescription | Type: Human prescription drug label
Date: 20070424

PIPRACIL®
(piperacillin for injection)
For Intravenous and Intramuscular Use

Rx only

To reduce the development of drug-resistant bacteria and maintain the effectiveness of PIPRACIL and other antibacterial drugs, PIPRACIL should only be used to treat or prevent infections that are proven or strongly suspected to be caused by bacteria.

DESCRIPTION

PIPRACIL, sterile piperacillin sodium, is a semisynthetic broad-spectrum penicillin for parenteral use derived from D(-)-α-aminobenzylpenicillin. The chemical name of piperacillin sodium is sodium (2S,5R,6R)-6-[(R)-2-(4-ethyl-2,3-dioxo-1-piperazinecarboxamido)-2-phenylacetamido]-3,-3-dimethyl-7-oxo-4-thia-1-azabicyclo[3.2.0]heptane-2-carboxylate. The chemical formula is C23H26N5NaO7S, and the molecular weight is 539.54. Its structural formula is:

Piperacillin sodium powder is a white to off-white solid having the characteristic appearance of products prepared by freeze-drying. It is freely soluble in water and in alcohol. The pH of an aqueous solution containing 400 milligrams per milliliter ranges from 5.5 to 7.5. One g contains 1.85 mEq (42.5 mg) of sodium (Na^+).

CLINICAL PHARMACOLOGY

Intravenous Administration:

In healthy adult volunteers, mean serum piperacillin concentrations immediately after a two‑to three‑minute intravenous injection of 2, 4, or 6 g were 305, 412, and 775 μg/mL, respectively. Serum concentrations lack dose proportionality.

PIPERACILLIN SERUM CONCENTRATIONS IN ADULTS (μg/mL) AFTER A TWO- TO THREE-MINUTE I.V. INJECTION
DOSE | 0 | 10 min | 20 min | 30 min | 1 h | 1.5 h | 2 h | 3 h | 4 h | 6 h | 8 h
2 | 305 (159- 615) | 202 (164- 225) | 156 (52- 165) | 67 (41- 88) | 40 (25- 57) | 24 (18- 31) | 20 (14- 24) | 8 (3- 11) | 3 (2- 4) | 2 (≤0.6- 3) | —
4 | 412 (389- 484) | 344 (315- 379) | 295 (269- 330) | 117 (98- 138) | 93 (78- 110) | 60 (50- 67) | 36 (26- 51) | 20 (17- 24) | 8 (7- 11) | 4 (3.7- 4.1) | 0.9 (0.7- 1)
6 | 775 (695- 849) | 609 (530- 670) | 563 (492- 630) | 325 (292- 363) | 208 (180- 239) | 138 (115- 175) | 90 (71- 113) | 38 (29- 53) | 33 (25- 44) | 8 (3- 19) | 3.2 (<2- 6)
PIPERACILLIN SERUM CONCENTRATIONS IN ADULTS (μg/mL) AFTER A 30-MINUTE I.V. INFUSION
DOSE | 0 | 5 min | 10 min | 15 min | 30 min | 45 min | 1 h | 1.5 h | 2 h | 4 h | 6 h | 7.5 h
4 | 244 (155- 298) | 215 (169- 247) | 186 (140- 209) | 177 (142- 213) | 141 (122-156) | 146 (110- 265) | 105 (85- 133) | 72 (53- 105) | 53 (36- 69) | 15 (6- 24) | 4 (1- 9) | 2 (0.5- 3)
6 | 353 (324- 371) | 298 (242- 339) | 298 (232- 331) | 272 (219-314) | 229 (185- 249) | 180 (144- 209) | 149 (117- 171) | 104 (89- 113) | 73 (66- 94) | 22 (12- 39) | 16 (5- 49) | — —

A 30-minute infusion of 6 g every 6 h gave, on the fourth day, a mean peak serum concentration of 420 μg/mL.

Intramuscular Administration:

PIPRACIL is rapidly absorbed after intramuscular injection. In healthy volunteers, the mean peak serum concentration occurs approximately 30 minutes after a single dose of 2 g and is about 36 μg/mL. The oral administration of 1 g probenecid before injection produces an increase in piperacillin peak serum level of about 30%. The area under the curve (AUC) is increased by approximately 60%.

Pharmacokinetics:

PIPRACIL is not absorbed when given orally. Peak serum concentrations are attained approximately 30 minutes after intramuscular injections and immediately after completion of intravenous injection or infusion. The serum half-life in healthy volunteers ranges from 36 minutes to one hour and 12 minutes. The mean elimination half-life of PIPRACIL in healthy adult volunteers is 54 minutes following administration of 2 g and 63 minutes following 6 g. As with other penicillins, PIPRACIL is eliminated primarily by glomerular filtration and tubular secretion; it is excreted rapidly as unchanged drug in high concentrations in the urine. Approximately 60% to 80% of the administered dose is excreted in the urine in the first 24 hours. Piperacillin urine concentrations, determined by microbioassay, are as high as 14,100 μg/mL following a 6-g intravenous dose and 8,500 μg/mL following a 4-g intravenous dose. These urine drug concentrations remain well above 1,000 μg/mL throughout the dosing interval.

Distribution:

PIPRACIL binding to human serum proteins is 16%. The drug is widely distributed in human tissues and body fluids, including bone, prostate, and heart, and reaches high concentrations in bile. After a 4-g bolus injection, maximum biliary concentrations average 3,205 μg/mL. It penetrates into the cerebrospinal fluid in the presence of inflamed meninges.

Special Populations:

Renal Insufficiency: The elimination half-life is increased twofold in mild to moderate renal impairment and fivefold to sixfold in severe impairment. Because PIPRACIL is excreted by the biliary route as well as by the renal route, it can be used safely in appropriate dosage in patients with severely restricted kidney function. (See DOSAGE AND ADMINISTRATION.)

Pediatric Patients: After intravenous administration of 50 mg/kg (5-minute infusion) in neonates, the mean plasma concentration of piperacillin extrapolated to time zero was 141 μg/mL, and the apparent volume of distribution averaged 101 mL/kg.

In premature neonates, the mean elimination half-life has been reported to range from 147 to 258 minutes following administration of a single intravenous dose of 75 mg/kg, the half‑life decreasing with increasing postnatal age. The changes in half-life appeared to be caused by an immature renal system during the first weeks of life. In one study in neonates, the mean elimination half-life ranged from 127 to 217 minutes following a single intravenous dose of 50 mg/kg. As in premature neonates, the half-life in neonates decreased with increasing postnatal age. The mean total body clearance in neonates has been reported to range from 32 to 41 mL/min/1.73 m^2 after an intravenous dose of 50 mg/kg.

Following administration of an intravenous dose of 50 mg/kg in older pediatric patients (from 1 month up to 15 years of age), the mean elimination half-life has been reported to range from 31 to 37 minutes, and the mean total body clearance has been reported to range from 124 to 160 mL/min/1.73 m^2.

As in adults, PIPRACIL elimination tends to be prolonged in pediatric patients with renal impairment. In one study in pediatric patients (age range, 3.3 to 14.3 years), the mean elimination half-life in patients with decreased renal function was approximately 60 minutes versus 37 minutes in patients with normal renal function. The elimination half-life has been reported to range from 3.5 to 14 hours in neonates with severe renal impairment.

Pharmacokinetic data have indicated that among pediatric patients below 12 years of age, those with cystic fibrosis have increased bioavailability, lower serum concentrations, and increased total body clearance of piperacillin compared to young, healthy pediatric volunteers under 12 years of age.

MICROBIOLOGY

Piperacillin is an antibiotic which exerts its bactericidal activity by inhibiting both septum and cell wall synthesis. It is active against a variety of gram-positive and gram-negative aerobic and anaerobic bacteria. Piperacillin has been shown to be active against most strains of the following microorganisms, both in vitro and in clinical infections as described in the INDICATIONS AND USAGE section.

Aerobic gram-positive microorganisms
Enterococci, including Enterococcus faecalis
Streptococcus pneumoniae
Streptococcus pyogenes

Aerobic gram-negative microorganisms
Acinetobacter species
Enterobacter species
Escherichia coli
Haemophilus influenzae (non-β-lactamase-producing strains)
Klebsiella species
Morganella morganii
Neisseria gonorrhoeae
Proteus mirabilis
Proteus vulgaris
Providencia rettgeri
Pseudomonas aeruginosa
Serratia species

Anaerobic gram-positive microorganisms
Anaerobic cocci
Clostridium species

Anaerobic gram-negative microorganisms
Bacteroides species, including Bacteroides fragilis

The following in vitro data are available, but their clinical significance is unknown.

At least 90% of the following microorganisms exhibit an in vitro minimum inhibitory concentration (MIC) less than or equal to the susceptible breakpoint for piperacillin. However, the safety and effectiveness of piperacillin in treating clinical infections due to these microorganisms have not been established in adequate and well-controlled clinical trials.

Aerobic gram-positive microorganisms
Streptococcus agalactiae
Streptococcus bovis
Viridans group streptococci

Aerobic gram-negative microorganisms
Burkholderia cepacia
Citrobacter diversus
Citrobacter freundii
Pseudomonas fluorescens
Stenotrophomonas maltophilia
Yersinia enterocolitica

Anaerobic gram-positive microorganisms
Actinomyces species
Eubacterium species

Anaerobic gram-negative microorganisms
Fusobacterium necrophorum
Fusobacterium nucleatum
Porphyromonas asaccharolytica
Prevotella melaninogenica
Veillonella species

Susceptibility Testing Methods

Dilution Techniques:

Quantitative methods are used to determine antimicrobial minimum inhibitory concentrations (MICs). These MICs provide estimates of the susceptibility of bacteria to antimicrobial compounds. The MICs should be determined using a standardized procedure. Standardized procedures are based on a dilution method1,2 (broth or agar) or equivalent with standardized inoculum concentrations and standardized concentrations of piperacillin powder. The MIC values should be interpreted according to the following criteria:

For testingEnterobacteriaceae and Acinetobacter species:

MIC (μg/mL) | Interpretation
≤ 16 32-64 ≥ 128 | Susceptible (S) Intermediate (I) Resistant (R)

For testing Pseudomonas aeruginosa:

MIC (μg/mL) | Interpretation
≤ 64 ≥ 128 | Susceptible (S) Resistant (R)

For testing Enterococcus faecalisa:

MIC (μg/mL) | Interpretation
≤ 8 ≥ 16 | Susceptible (S) Resistant (R)
a Penicillin susceptibility may be used to predict the susceptibility to piperacillin.1,2

Haemophilus species are considered susceptible if the MIC of piperacillin is≤ to 1 μg/mL.*

* Dilution methods such as those described in the International Collaborative Study (Acta Pathol Microbiol Scand [B] 1971; suppl 217) have been used to determine susceptibility of organisms to piperacillin.

Dilution (MICs) susceptibility test methods and interpretative criteria for assessing the susceptibility of Neisseria gonorrhoeae to piperacillin have not been established. However,β‑lactamase testing will detect one form of penicillin resistance in Neisseria gonorrhoeae and is recommended.1,2

Dilution (MICs) susceptibility test methods and interpretative criteria for assessing the susceptibility of Streptococcus pneumoniae and Streptococcus pyogenes to piperacillin have not been established.1,2

A report of“Susceptible” indicates that the pathogen is likely to be inhibited if the antimicrobial compound in the blood reaches the concentrations usually achievable. A report of “Intermediate” indicates that the result should be considered equivocal, and, if the microorganism is not fully susceptible to alternative, clinically feasible drugs, the test should be repeated. This category implies possible clinical applicability in body sites where the drug is physiologically concentrated or in situations where high dosage of drug can be used. This category also provides a buffer zone which prevents small uncontrolled technical factors from causing major discrepancies in interpretation. A report of “Resistant” indicates that the pathogen is not likely to be inhibited if the antimicrobial compound in the blood reaches the concentrations usually achievable; other therapy should be selected.

Quality Control:

Standardized susceptibility test procedures require the use of laboratory control microorganisms to control the technical aspects of the laboratory procedures. Standard piperacillin powder should provide the following MIC values:

Microorganism |  | MIC (μg/mL)
Enterococcus faecalis Escherichia coli Pseudomonas aeruginosa | ATCC 29212 ATCC 25922 ATCC 27853 | 1-4 1-4 1-8

Diffusion Techniques:

Quantitative methods that require measurement of zone diameters also provide reproducible estimates of the susceptibility of bacteria to antimicrobial compounds. One such standardized procedure2,3 requires the use of standardized inoculum concentrations. This procedure uses paper disks impregnated with 100μg of piperacillin to test the susceptibility of microorganisms to piperacillin.

Reports from the laboratory providing results of the standard single-disk susceptibility test with a 100 μg piperacillin disk should be interpreted according to the following criteria:

For testing Enterobacteriaceae and Acinetobacter species:

Zone Diameter (mm) | Interpretation
≥ 21 18-20 ≤ 17 | Susceptible (S) Intermediate (I) Resistant (R)

For testing Pseudomonas aeruginosa:

Zone Diameter (mm) | Interpretation
≥ 18 ≤ 17 | Susceptible (S) Resistant (R)

For testing Enterococcus faecalisb:

Zone Diameter (mm) | Interpretation
≥ 15 ≤ 14 | Susceptible (S) Resistant (R)
b Penicillin susceptibility may be used to predict the susceptibility to piperacillin.2,3

Haemophilus species which give zones of ≥ 29 mm are susceptible; resistant strains give zones of ≤ 28 mm. The above interpretive criteria are based on the use of the standardized procedure. Antibiotic susceptibility testing requires carefully prescribed procedures. Susceptibility tests are biased to a considerable degree when different methods are used.

NCCLS Approved Standard; M2-A2 (Formerly ASM-2) Performance Standards for Antimicrobic Disk Susceptibility Tests, Second Edition, available from the National Committee of Clinical Laboratory Standards.

Disk diffusion (zone diameters) susceptibility test methods and interpretative criteria for assessing the susceptibility of Neisseria gonorrhoeae to piperacillin have not been established. However, β-lactamase testing to penicillin is recommended. It will detect one form of penicillin resistance, chromosomally mediated resistance, in Neisseria gonorrhoeae. In addition, gonococci with 10-unit penicillin disk zone diameters of ≤ 19 mm are likely to be β-lactamase producing strains (plasmid-mediated penicillin resistance).2,3

Disk diffusion (zone diameters) susceptibility test methods and interpretative criteria for assessing the susceptibility of Streptococcus pneumoniae and Streptococcus pyogenes to piperacillin have not been established.2,3

Interpretation should be as stated above for results using dilution techniques. Interpretation involves correlation of the diameter obtained in the disk test with the MIC for piperacillin.

Quality Control:
As with standardized dilution techniques, diffusion methods require the use of laboratory control microorganisms that are used to control the technical aspects of the laboratory procedures. For the diffusion technique, the 100-μg piperacillin disk should provide the following zone diameters in these laboratory test quality control strains:

Microorganism |  | Zone Diameter (mm)
Escherichia coli Pseudomonas aeruginosa | ATCC 25922 ATCC 27853 | 24-30 25-33

Anaerobic Techniques:

For anaerobic bacteria, the susceptibility to piperacillin as MICs can be determined by standardized test methods.4 The MIC values obtained should be interpreted according to the following criteria:

MIC (μg/mL) | Interpretation
≤ 32 64 ≥ 128 | Susceptible (S) Intermediate (I) Resistant (R)

Interpretation is identical to that stated above for results using dilution techniques.

As with other susceptibility techniques, the use of laboratory control microorganisms is required to control the technical aspects of the laboratory standardized procedures. Standardized piperacillin powder should provide the following MIC values:

Microorganism |  | MIC (μg/mL)
Bacteroides fragilisc Bacteroides thetaiotaomicrond | ATCC 25285 ATCC 29741 | 2-8 8-32
c This quality control range is applicable only to tests performed using either Brucella blood agar or Wilkins-Chalgren agar with the Reference Agar Dilution Method.4
d This quality range is applicable only to tests performed in the broth formulation of Wilkins-Chalgren agar with the Broth microdilution method.4

INDICATIONS AND USAGE

Therapeutic: PIPRACIL is indicated for the treatment of serious infections caused by susceptible strains of the designated microorganisms in the conditions listed below:

Intra-Abdominal Infections including hepatobiliary and surgical infections caused by E. coli, Pseudomonas aeruginosa, enterococci, Clostridium spp., anaerobic cocci, or Bacteroides spp., including B. fragilis.

Urinary Tract Infections caused by E. coli, Klebsiella spp., P. aeruginosa, Proteus spp., including P. mirabilis, or enterococci.

Gynecologic Infections including endometritis, pelvic inflammatory disease, pelvic cellulitis caused by Bacteroides spp., including B. fragilis, anaerobic cocci, Neisseria gonorrhoeae, or enterococci (E. faecalis).

Septicemia including bacteremia caused by E. coli, Klebsiella spp., Enterobacter spp., Serratia spp., P. mirabilis, S. pneumoniae, enterococci, P. aeruginosa, Bacteroides spp., or anaerobic cocci.

Lower RespiratoryTract Infections caused by E. coli, Klebsiella spp., Enterobacter spp., P. aeruginosa, Serratia spp., H. influenzae, Bacteroides spp., or anaerobic cocci. Although improvement has been noted in patients with cystic fibrosis, lasting bacterial eradication may not necessarily be achieved.

Skin and Skin Structure Infections caused by E. coli, Klebsiella spp., Serratia spp., Acinetobacter spp., Enterobacter spp., P. aeruginosa, Morganella morganii, Providencia rettgeri, Proteus vulgaris, P. mirabilis, Bacteroides spp., including B. fragilis, anaerobic cocci, or enterococci.

Bone and Joint Infections caused by P. aeruginosa, enterococci, Bacteroides spp., or anaerobic cocci.

Uncomplicated Gonococcal Urethritis caused by N. gonorrhoeae.

PIPRACIL has also been shown to be clinically effective for the treatment of infections at various sites caused by Streptococcus species including S. pyogenes and S. pneumoniae; however, infections caused by these organisms are ordinarily treated with more narrow spectrum penicillins. Because of its broad spectrum of bactericidal activity against gram-positive and gram-negative aerobic and anaerobic bacteria, PIPRACIL is particularly useful for the treatment of mixed infections and presumptive therapy prior to the identification of the causative organisms.

Also, PIPRACIL may be administered as single drug therapy in some situations where normally two antibiotics might be employed.

Piperacillin has been successfully used with aminoglycosides, especially in patients with impaired host defenses. Both drugs should be used in full therapeutic doses.

Appropriate cultures should be made for susceptibility testing before initiating therapy and therapy adjusted, if appropriate, once the results are known.

Prophylaxis: PIPRACIL is indicated for prophylactic use in surgery including intra-abdominal (gastrointestinal and biliary) procedures, vaginal hysterectomy, abdominal hysterectomy, and cesarean section. Effective prophylactic use depends on the time of administration; PIPRACIL should be given one-half to one hour before the operation so that effective levels can be achieved in the site prior to the procedure.

The prophylactic use of piperacillin should be stopped within 24 hours, since continuing administration of any antibiotic increases the possibility of adverse reactions, but in the majority of surgical procedures, does not reduce the incidence of subsequent infections. If there are signs of infection, specimens for culture and susceptibility testing should be obtained for identification of the causative microorganism so that appropriate therapy can be instituted.

To reduce the development of drug-resistant bacteria and maintain the effectiveness of PIPRACIL and other antibacterial drugs, PIPRACILshould only be used to treat or prevent infections that are proven or strongly suspected to be caused by susceptible bacteria. When culture and susceptibility information are available, they should be considered in selecting or modifying antibacterial therapy. In the absence of such data, local epidemiology and susceptibility patterns may contribute to the empiric selection of therapy.

CONTRAINDICATIONS

PIPRACIL is contraindicated in patients with a history of allergic reactions to any of the betalactams, including penicillins and/or cephalosporins.

WARNINGS

SERIOUS AND OCCASIONALLY FATAL HYPERSENSITIVITY (ANAPHYLACTIC/ANAPHYLACTOID) REACTIONS HAVE BEEN REPORTED IN PATIENTS ON PENICILLIN THERAPY. THESE REACTIONS ARE MORE LIKELY TO OCCUR IN INDIVIDUALS WITH A HISTORY OF PENICILLIN HYPERSENSITIVITY AND/OR A HISTORY OF SENSITIVITY TO MULTIPLE ALLERGENS. THERE HAVE BEEN REPORTS OF INDIVIDUALS WITH A HISTORY OF PENICILLIN HYPERSENSITIVITY WHO HAVE EXPERIENCED SEVERE REACTIONS WHEN TREATED WITH CEPHALOSPORINS. BEFORE INITIATING THERAPY WITH PIPRACIL, CAREFUL INQUIRY SHOULD BE MADE CONCERNING PREVIOUS HYPERSENSITIVITY REACTIONS TO PENICILLINS, CEPHALOSPORINS OR OTHER ALLERGENS. IF AN ALLERGIC REACTION OCCURS, PIPRACIL SHOULD BE DISCONTINUED AND APPROPRIATE THERAPY INSTITUTED. SERIOUS ANAPHYLACTIC/ANAPHYLACTOID REACTIONS REQUIRE IMMEDIATE EMERGENCY TREATMENT WITH EPINEPHRINE. OXYGEN, INTRAVENOUS STEROIDS AND AIRWAY MANAGEMENT, INCLUDING INTUBATION, SHOULD ALSO BE ADMINISTERED AS INDICATED.

Clostridium difficile associated diarrhea (CDAD) has been reported with use of nearly all antibacterial agents, including PIPRACIL, and may range in severity from mild diarrhea to fatal colitis. Treatment with antibacterial agents alters the normal flora of the colon leading to overgrowth of C. difficile.

C. difficile produces toxins A and B which contribute to the development of CDAD. Hypertoxin producing strains of C. difficile cause increased morbidity and mortality, as these infections can be refractory to antimicrobial therapy and may require colectomy. CDAD must be considered in all patients who present with diarrhea following antibiotic use. Careful medical history is necessary since CDAD has been reported to occur over two months after the administration of antibacterial agents.

If CDAD is suspected or confirmed, ongoing antibiotic use not directed against C. difficile may need to be discontinued. Appropriate fluid and electrolyte management, protein supplementation, antibiotic treatment of C. difficile, and surgical evaluation should be instituted as clinically indicated.

PRECAUTIONS

General

Bleeding manifestations have occurred in some patients receiving β-lactam antibiotics, including piperacillin. These reactions have sometimes been associated with abnormalities of coagulation tests such as clotting time, platelet aggregation, and prothrombin time and are more likely to occur in patients with renal failure.

If bleeding manifestations occur, the antibiotic should be discontinued and appropriate therapy instituted.

The possibility of the emergence of resistant organisms which might cause superinfections should be kept in mind, particularly during prolonged treatment. If this occurs, appropriate measures should be taken.

As with other penicillins, patients may experience neuromuscular excitability or convulsions if higher than recommended doses are given intravenously.

PIPRACIL is a monosodium salt containing 1.85 mEq of Na^+ per g (42.5 mg of Na^+ per g). This should be considered when treating patients requiring restricted salt intake. Periodic electrolyte determinations should be made in patients with low potassium reserves, and the possibility of hypokalemia should be kept in mind with patients who have potentially low potassium reserves and who are receiving cytotoxic therapy or diuretics.

Leukopenia and neutropenia may occur during prolonged therapy.

As with other semisynthetic penicillins, PIPRACIL therapy has been associated with an increased incidence of fever and rash in cystic fibrosis patients.

Prescribing PIPRACIL in the absence of a proven or strongly suspected bacterial infection or a prophylactic indication is unlikely to provide benefit to the patient and increases the risk of the development of drug-resistant bacteria.

Information for Patients

Patients should be counseled that antibacterial drugs including PIPRACIL should only be used to treat bacterial infections. They do not treat viral infections (eg, the common cold). When PIPRACIL is prescribed to treat a bacterial infection, patients should be told that although it is common to feel better early in the course of therapy, the medication should be taken exactly as directed. Skipping doses or not completing the full course of therapy may (1) decrease the effectiveness of the immediate treatment and (2) increase the likelihood that bacteria will develop resistance and will not be treatable by PIPRACIL or other antibacterial drugs in the future.

Diarrhea is a common problem caused by antibiotics which usually ends when the antibiotic is discontinued. Sometimes after starting treatment with antibiotics, patients can develop watery and bloody stools (with or without stomach cramps and fever) even as late as two or more months after having taken the last dose of antibiotic. If this occurs, patients should contact their physician as soon as possible.

Laboratory Tests

While piperacillin possesses the characteristic low toxicity of the penicillin group of antibiotics, periodic assessment of organ system functions, including renal, hepatic, and hematopoietic, during prolonged therapy is advisable.

All patients with gonorrhea should have a serologic test for syphilis at the time of diagnosis. Patients treated with piperacillin should have a follow-up serologic test for syphilis after 3 months.

Drug Interactions

Aminoglycosides

The mixing of piperacillin with an aminoglycoside in vitro can result in substantial inactivation of the aminoglycoside.

Vecuronium

When used in the perioperative period, piperacillin has been implicated in the prolongation of the neuromuscular blockade of vecuronium. Caution is indicated when piperacillin is used perioperatively. In one controlled clinical study, the ureidopenicillins, including piperacillin, were reported to prolong the action of vecuronium. Due to their similar mechanism of action, it is expected that the neuromuscular blockade produced by any of the non-depolarizing muscle relaxants could be prolonged in the presence of piperacillin.

Probenecid

The oral combination of probenecid before intramuscular injection of PIPRACIL produces an increase in piperacillin peak serum level of about 30%.

Anticoagulants

Coagulation parameters should be tested more frequently and monitored regularly during simultaneous administration of high doses of heparin, oral anticoagulants, or other drugs that may affect the blood coagulation system or the thrombocyte function.

Methotrexate

Piperacillin sodium may reduce the excretion of methotrexate. Therefore, serum levels of methotrexate should be monitored in patients to avoid drug toxicity.

Drug/Laboratory Test Interactions

As with other penicillins, the administration of PIPRACIL may result in a false-positive reaction for glucose in the urine using a copper-reduction method. It is recommended that glucose tests based on enzymatic glucose oxidase reactions be used.

There have been reports of positive test results using the Bio-Rad Laboratories Platelia Aspergillus EIA test in patients receiving piperacillin/tazobactam injection who were subsequently found to be free of Aspergillus infection. Cross-reactions with non-Aspergillus polysaccharides and polyfuranoses with the Bio-Rad Laboratories Platelia Aspergillus EIA test have been reported.

Therefore, positive test results in patients receiving piperacillin should be interpreted cautiously and confirmed by other diagnostic methods.

Carcinogenesis, Mutagenesis, Impairment of Fertility

Carcinogenesis

Long-term studies in animals have not been performed to evaluate carcinogenic potential.

Mutagenesis

Piperacillin was negative in the Ames Salmonella reversion test at concentrations up to 10 μg/plate. There was no DNA damage in bacteria (Rec assay) exposed to piperacillin at concentrations up to 200 μg/disc. In a mammalian point mutation (mouse lymphoma cells) assay, piperacillin was positive at concentrations ≥ 2500 μg/mL. Piperacillin was negative in a cell (BALB/c-3T3) transformation assay at concentrations up to 3000 μg/mL. In vivo, piperacillin did not induce chromosomal aberrations in the bone marrow cells of mice at I.V. doses up to 2000 mg/kg/day or rats at I.V. doses up to 1500 mg/kg/day. These doses are half (mice) or three‑fourths (rats) the maximum recommended human daily dose based on body-surface area (mg/m^2). In another in vivo test, there was no dominant lethal effect when piperacillin was administered to rats at I.V. doses up to 2000 mg/kg/day, which is similar to the maximum recommended human daily dose based on body-surface area (mg/m^2). When piperacillin was administered to mice at I.V. doses up to 2000 mg/kg/day, which is half the maximum recommended human daily dose based on body-surface area (mg/m^2), urine from these animals was not mutagenic when tested in the Ames assay using Salmonella strain TA-98 in the absence of β-glucuronidase.

Impairment of Fertility

Reproduction studies have been performed in mice (SQ) and rats (I.P.) and have revealed no evidence of impaired fertility due to piperacillin administered up to a dose which is half (mice) or similar (rats) to the maximum recommended human daily dose based on body-surface area (mg/m^2). The plasma/serum concentrations at the highest daily dose administered to rats in reproduction studies were comparable to the maximum serum concentration seen in man, based on a toxicology study in rats in which similar doses of piperacillin (in combination with a beta‑lactamase inhibitor, tazobactam) were administered I.P.and based on extrapolations from an animal pharmacokinetic study using lower doses of piperacillin alone.

Pregnancy

Teratogenic effects—Pregnancy Category B

Teratology studies have been performed in mice (I.V.) and rats (I.V., I.P. and SQ) and have revealed no evidence of harm to the fetus due to piperacillin administered up to a dose which is approximately half the maximum recommended human daily dose based on body-surface area (mg/m^2). In pharmacokinetic studies in pregnant and nonpregnant rats, in which piperacillin was administered I.V. at a dose which is half the maximum daily dose administered in teratology studies, serum concentrations in rats were approximately 10 times the maximum serum concentration seen in man. In other studies in mice and rats, in which piperacillin (in combination with a beta-lactamase inhibitor, tazobactam) was administered I.V. at approximately half the maximum daily dose administered in teratology studies, plasma concentrations of piperacillin were approximately 2 times (mice) and 5 times (rats) the serum concentrations seen in man.

There are, however, no adequate and well-controlled studies with piperacillin in pregnant women. Because animal reproduction studies are not always predictive of the human response, this drug should be used during pregnancy only if clearly needed.

Nursing Mothers

Piperacillin is excreted in low concentrations in human milk. Caution should be exercised when PIPRACIL is administered to nursing mothers.

Pediatric Use

Safety and effectiveness in pediatric patients have not been established.

Data from published pharmacokinetics studies indicate that the elimination half-life of piperacillin in neonates is twofold to fourfold longer than that seen in pediatric patients 1 month of age and above as well as in adults. In infants, children, and adolescents, the elimination half-life of piperacillin is shorter than that observed in adults. As in adults, the elimination of piperacillin is decreased in pediatric patients with renal impairment. (See CLINICAL PHARMACOLOGY.)

Geriatric Use

Clinical studies of PIPRACIL did not include sufficient numbers of subjects aged 65 and over to determine whether they respond differently from younger subjects.

In general, dose selection for an elderly patient should be cautious, usually starting at the low end of the dosing range, reflecting the greater frequency of decreased hepatic, renal, or cardiac function, and of concomitant disease or other drug therapy.

PIPRACIL contains 42.5 mg (1.85 mEq) of sodium per gram. At the usual recommended doses, patients would receive between 255 and 765 mg/day (11.1 and 33.3 mEq) of sodium. The geriatric population may respond with a blunted natriuresis to salt loading. The total sodium content from dietary and non-dietary sources may be clinically important with regard to such diseases as congestive heart failure.

This drug is known to be substantially excreted by the kidney, and the risk of toxic reactions to this drug may be greater in patients with impaired renal function. Because elderly patients are more likely to have decreased renal function, care should be taken in dose selection, and it may be useful to monitor renal function.

ADVERSE REACTIONS

PIPRACIL is generally well tolerated. The most common adverse reactions have been local in nature, following intravenous or intramuscular injection. The following adverse reactions may occur:

Local Reactions: In clinical trials thrombophlebitis was noted in 4% of patients. Pain, erythema, and/or induration at the injection site occurred in 2% of patients. Less frequent reactions including ecchymosis, deep vein thrombosis, and hematomas have also occurred.

Gastrointestinal: Diarrhea and loose stools were noted in 2% of patients. Other less frequent reactions included vomiting, nausea, increases in liver enzymes (LDH, AST, ALT), hyperbilirubinemia, cholestatic hepatitis, bloody diarrhea, and pseudomembranous colitis. The onset of pseudomembranous colitis symptoms may occur during or after antibiotic treatment. (See WARNINGS.)

Hypersensitivity Reactions: Anaphylactic/anaphylactoid reactions (some leading to shock and fatalities) have been reported. (See WARNINGS.)

Rash was noted in 1% of patients. Other less frequent findings included pruritus, vesicular eruptions, and positive Coombs tests.

Other dermatologic manifestations, such as erythema multiforme, urticaria, toxic epidermal necrolysis and Stevens-Johnson syndrome, have been reported.

Renal: Elevations of creatinine or BUN, renal failure and interstitial nephritis have been reported.

Central Nervous System: Headache, dizziness, fatigue, and seizures have been reported.

Hemic and Lymphatic: Hemolytic anemia, agranulocytosis, pancytopenia, prolonged bleeding time, reversible leukopenia, neutropenia, thrombocytopenia, and/or eosinophilia have been reported. As with other β-lactam antibiotics, reversible leukopenia (neutropenia) is more apt to occur in patients receiving prolonged therapy at high dosages or in association with drugs known to cause this reaction.

Serum Electrolytes: Individuals with liver disease or individuals receiving cytotoxic therapy or diuretics were reported to demonstrate a decrease in serum potassium concentrations with high doses of piperacillin. Hypokalemia has been reported.

Skeletal: Prolonged muscle relaxation (see PRECAUTIONS, Drug Interactions).

Other: Fever, superinfection, including candidiasis; hemorrhagic manifestations have been reported.

Piperacillin therapy has been associated with an increased incidence of fever and rash in cystic fibrosis patients.

OVERDOSAGE

There is no specific information on overdose with PIPRACIL. Other penicillin-class drugs in overdosage, however, have the potential to cause neuromuscular hyperirritability or convulsive seizures. In case of overdosage, discontinue medication, treat symptomatically, and institute supportive measures as required. Piperacillin can be removed by hemodialysis but not peritoneal dialysis.

DOSAGE AND ADMINISTRATION

PIPRACIL may be administered by the intramuscular route (see NOTE) or intravenously as a three- to five-minute intravenous injection or as a 20- to 30-minute infusion. The usual dosage of PIPRACIL for serious infections is 3 to 4 g given every four to six hours as a 20- to 30-minute infusion. For serious infections, the intravenous route should be used.

PIPRACIL should not be mixed with an aminoglycoside in a syringe or infusion bottle since this can result in inactivation of the aminoglycoside.

The maximum daily dose for adults is usually 24 g/day, although higher doses have been used.

Intramuscular injections (see NOTE) should be limited to 2 g per injection site. This route of administration has been used primarily in the treatment of patients with uncomplicated gonorrhea and urinary tract infections.

DOSAGE RECOMMENDATIONS
Type of Infection | Usual Total Daily Dose
Serious infections such as septicemia, nosocomial pneumonia, intra-abdominal infections, aerobic and anaerobic gynecologic infections, and skin and soft tissue infections | 12 – 18 g/d I.V. (200 – 300 mg/kg/d) in divided doses every 4 to 6 h
Complicated urinary tract infections | 8 – 16 g/d I.V. (125 – 200 mg/kg/d) in divided doses every 6 to 8 h
Uncomplicated urinary tract infections and most community-acquired pneumonia | 6 – 8 g/d I.M. or I.V. (100– 125 mg/kg/d) in divided doses every 6 to 12 h
Uncomplicated gonorrhea infections | 2 g I.M.† as a one-time dose
†One g of probenecid should be given orally one-half hour prior to injection.

The average duration of PIPRACIL treatment is from seven to ten days, except in the treatment of gynecologic infections, which is from three to ten days; the duration should be guided by the patient's clinical and bacteriological progress. For most acute infections, treatment should be continued for at least 48 to 72 hours after the patient becomes asymptomatic. Antibiotic therapy for S. pyogenes infections should be maintained for at least ten days to reduce the risk of rheumatic fever.

When PIPRACIL is given concurrently with aminoglycosides, both drugs should be used in full therapeutic doses.

Renal Impairment

Dosage in Renal Impairment
Creatinine Clearance mL/min | Urinary Tract Infection (uncomplicated) | Urinary Tract Infection (complicated) | Serious Systemic Infection
>40 | No dosage adjustment necessary
20-40 | No dosage adjustment necessary | 9 g/day 3 g every 8 h | 12 g/day 4 g every 8 h
<20 | 6 g/day 3 g every 12 h | 6 g/day 3 g every 12 h | 8 g/day 4 g every 12 h

For patients on hemodialysis, the maximum daily dose is 6 g/day (2 g every 8 hours). In addition, because hemodialysis removes 30% to 50% of piperacillin in 4 hours, a 1-g additional dose should be administered following each dialysis period.

For patients with renal failure and hepatic insufficiency, measurement of serum levels of piperacillin will provide additional guidance for adjusting dosage.

Prophylaxis

When possible, PIPRACIL should be administered as a 20- to 30-minute infusion just prior to anesthesia. Administration while the patient is awake will facilitate identification of possible adverse reactions during drug infusion. (See PRECAUTION, Drug Interactions.)

INDICATION | 1st Dose | 2nd Dose | 3rd Dose
Intra-abdominal Surgery | 2 g I.V. just prior to surgery | 2 g during surgery | 2 g every 6 h Post-Op for no more than 24 h
Vaginal Hysterectomy | 2 g I.V. just prior to surgery | 2 g 6 h after 1st dose | 2 g 12 h after 1st dose
Cesarean Section | 2 g I.V. after cord is clamped | 2 g 4 h after 1st dose | 2 g 8 h after 1st dose
Abdominal Hysterectomy | 2 g I.V. just prior to surgery | 2 g on return to recovery room | 2 g after 6 h

Pediatric patients. Dosages in pediatric patients under 12 years of age have not been studied in adequate and well-controlled clinical trials (See CLINICAL PHARMACOLOGY).

PRODUCT RECONSTITUTION/DOSAGE PREPARATION

Conventional Vials:

Diluents for Reconstitution

Sterile Water for Injection
Bacteriostatic¶ Water for Injection

Sodium Chloride Injection
Bacteriostatic¶ Sodium Chloride Injection
Dextrose 5% in Water
Dextrose 5% and 0.9% Sodium Chloride
Lidocaine# HCl 0.5-1% (without epinephrine)

¶Either Parabens or Benzyl Alcohol.
#For Intramuscular Use Only. Lidocaine is contraindicated in patients with a known history of hypersensitivity to local anesthetics of the amide type.

Conventional Vials:
Intravenous Solutions | Intravenous Admixtures
Dextrose 5% in Water 0.9% Sodium Chloride Dextrose 5% and 0.9% Sodium Chloride Lactated Ringer's Injection†† Dextran 6% in 0.9% Sodium Chloride | Normal Saline [+ KCl 40 mEq] 5% Dextrose in Water [+ KCl 40 mEq] 5% Dextrose/Normal Saline [+ KCl 40 mEq] Ringer's Injection [+ KCl 40 mEq] Lactated Ringer's Injection [+ KCl 40 mEq]††
††When PIPRACIL®is further diluted with Lactated Ringer's Injection, the diluted solution must be administered within 2 hours.

Intravenous Administration

Reconstitution Directions for Conventional Vials: Reconstitute each gram of PIPRACIL with at least 5 mL of a suitable diluent (except Lidocaine HCl 0.5%-1% without epinephrine) listed above. Shake well until dissolved. Reconstituted solution may be diluted to the desired volume (eg, 50 or 100 mL) in the above listed intravenous solutions and admixtures.

DIRECTIONS FOR ADMINISTRATION
Intermittent IV Infusion
Infuse diluted solution over period of about 30 minutes. During infusion, it is desirable to discontinue the primary intravenous solution.

Intravenous Injection (Bolus)
Reconstituted solution should be injected slowly over a 3-to 5-minute period to help avoid vein irritation.

Intramuscular Administration

(Conventional Vials Only)

Reconstitution Directions:Reconstitute each gram of PIPRACIL with 2 mL of a suitable diluent listed above to achieve a concentration of 1 g per 2.5 mL. Shake well until dissolved.

DIRECTIONS FOR ADMINISTRATION
When indicated by clinical and bacteriological findings, intramuscularadministration of 6 to 8 g daily of PIPRACIL, in divided doses, may be utilized for initiation of therapy. In addition, intramuscular administration of the drug may be considered for maintenance therapy after clinical and bacteriologic improvement has been obtained with intravenous piperacillin sodium treatment. Intramuscular administration should not exceed 2 g per injection at any one site.

The preferred site is the upper outer quadrant of the buttock (ie, gluteus maximus).

The deltoid area should be used only if well-developed, and then only with caution to avoid radial nerve injury. Intramuscular injections should not be made into the lower or mid-third of the upper arm.

Stability of PIPRACIL Following Reconstitution

PIPRACIL is stable in both glass and plastic containers when reconstituted with recommended diluents and when diluted with the intravenous solutions and intravenous admixtures indicated above.

Pharmacy vials should be used immediately after reconstitution. Discard any unused portion after 24 hours if stored at room temperature (20° to 25°C [68° to 77°F]), or after 48 hours if stored at refrigerated temperature (2° to 8°C [36° to 46°F]). Vials should not be frozen after reconstitution.

How Supplied

PIPRACIL® (piperacillin for injection) is available in vials containing freeze-dried piperacillin sodium powder equivalent to two, three, and four g of piperacillin. One g of piperacillin (as a monosodium salt) contains 1.85 mEq (42.5 mg) of sodium.

Product Numbers
2 gram/Vial-10 per box-NDC 0206-3879-16
3 gram/Vial-10 per box-NDC 0206-3882-55
4 gram/Vial-10 per box-NDC 0206-3880-25

Store at controlled room temperature 20°C-25°C(68°F-77°F).

REFERENCES

^1National Committee for Clinical Laboratory Standards. Methods for Dilution Antimicrobial Susceptibility Tests for Bacteria that Grow Aerobically – Fifth Edition. Approved Standard NCCLS Document M7-A5, Vol. 20, No. 2, NCCLS, Wayne, PA, January, 2000.

^2National Committee for Clinical Laboratory Standards. Performance Standards for Antimicrobial Susceptibility Testing – Eleventh Informational Supplement. NCCLS Document M100-S11, Vol. 21, No. 1, NCCLS, Wayne, PA, January, 2001.

^3National Committee for Clinical Laboratory Standards. Performance Standards for Antimicrobial Disk Susceptibility Tests – Seventh Edition. Approved Standard NCCLS Document M2-A7, Vol. 20, No. 1, NCCLS, Wayne, PA, January, 2000.

^4National Committee for Clinical Laboratory Standards. Methods for Antimicrobial Susceptibility Testing of Anaerobic Bacteria – Fifth Edition. Approved Standard NCCLS Document M11-A5, Vol. 21, No. 2, NCCLS, Wayne, PA, March, 2001.

Wyeth®

Wyeth Pharmaceuticals Inc.
Philadelphia, PA 19101

W10440C007
ET01
Rev 03/07